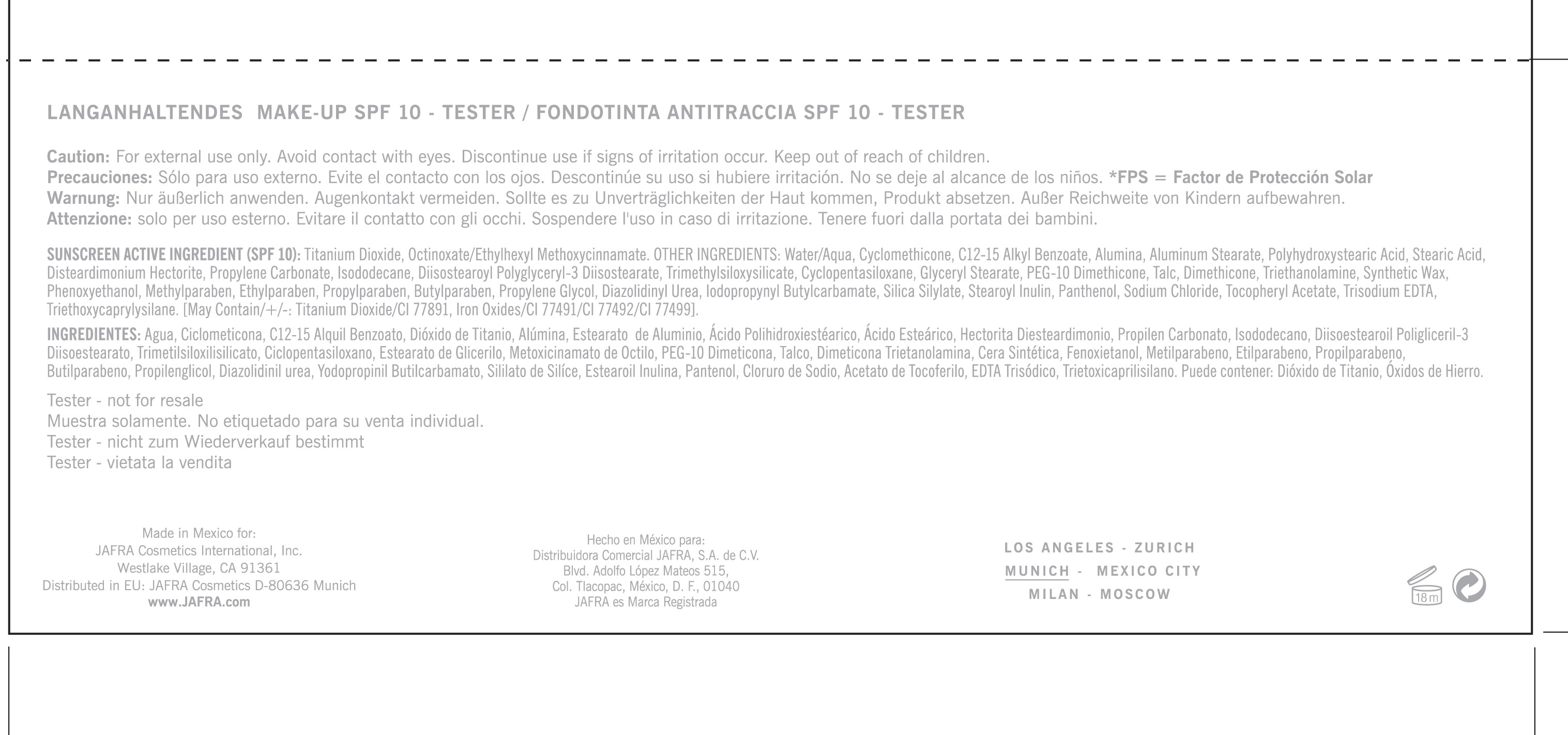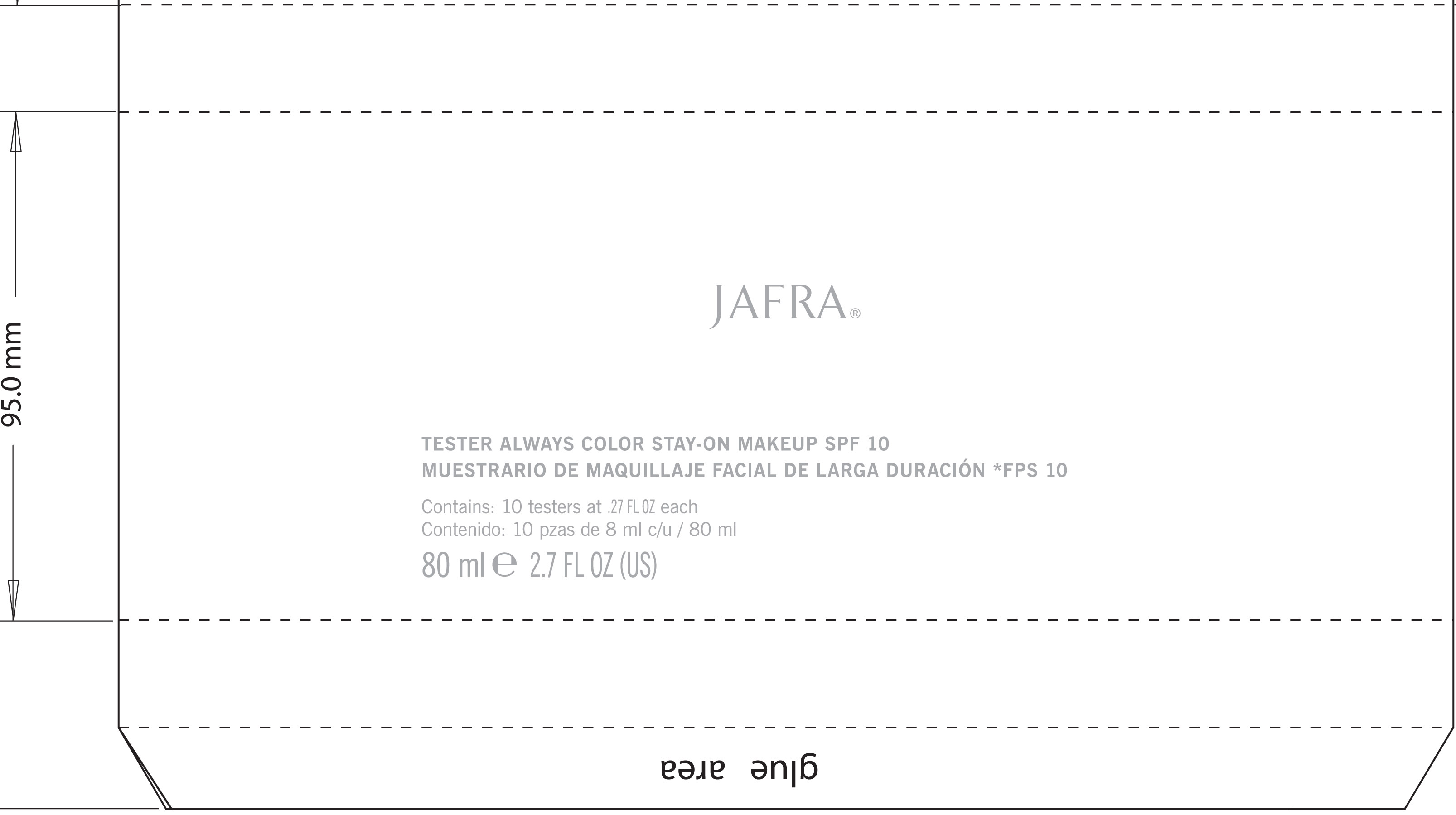 DRUG LABEL: Jafra
NDC: 68828-106 | Form: LIQUID
Manufacturer: Jafra Cosmetics International Inc
Category: prescription | Type: HUMAN PRESCRIPTION DRUG LABEL
Date: 20120828

ACTIVE INGREDIENTS: TITANIUM DIOXIDE 6.4 mL/80 mL; OCTINOXATE 2 mL/80 mL
INACTIVE INGREDIENTS: WATER; CYCLOMETHICONE; C12-15 ALKYL BENZOATE; ALUMINUM OXIDE; ALUMINUM STEARATE; POLYHYDROXYSTEARIC ACID (2300 MW); STEARIC ACID; PROPYLENE CARBONATE; ISODODECANE; CYCLOMETHICONE 5; GLYCERYL MONOSTEARATE; PEG-10 DIMETHICONE (600 CST); TALC; DIMETHICONE; TROLAMINE; SYNTHETIC WAX (1800 MW); PHENOXYETHANOL; METHYLPARABEN; ETHYLPARABEN; PROPYLPARABEN; BUTYLPARABEN; PROPYLENE GLYCOL; DIAZOLIDINYL UREA; IODOPROPYNYL BUTYLCARBAMATE; PANTHENOL; SODIUM CHLORIDE; ALPHA-TOCOPHEROL ACETATE; EDETATE TRISODIUM; TRIETHOXYCAPRYLYLSILANE; TITANIUM DIOXIDE; FERRIC OXIDE RED; FERRIC OXIDE YELLOW; FERROSOFERRIC OXIDE

Always Stay-on Makeup SPF 10 Med/Dark Testers

ACTIVE INGREDIENT

Sunscreen Active Ingredient (SPF 10): Titanium Dioxide, Octinoxate/Ethylhexyl Methoxycinnamate.

PURPOSE

Sunscreen

Keep out of reach of children

INDICATIONS AND USAGE

Discontinue use of signs of irritation occur

WARNINGS

Caution: For External Use only. Avoid contact with eyes.

DOSAGE AND ADMINISTRATION

no such information

INACTIVE INGREDIENT

Water/Aqua, Cyclomethicone, C12-15 Alkyl Benzoate, Alumina, Aluminum Stearate, Polyhydroxystearic Acid, Stearic Acid, Disteardimonium Hectorite, Propylene Carbonate, Isododecane, Diisostearyl Polyglyceryl-3 Diisostearate, Trimethylsiloxysilicate, Cyclopentasiloxane, Glyceryl stearate, PEG-10 Dimethicone, Talc, Dimethicone, Triethanolamine, Synthetic Wax, Phenoxyethanol, Methylparaben, Ethylparaben, Propylparaben, Butylparaben, Propylene Glycol, Diazolidinyl Urea, Iodopropynyl Butylcarbamate, Silica Silylate, Stearoyl inulin, panthenol, Sodium Chloride, Tocopheryl Acetate, Trisodium EDTA, Triethoxycaprylysilane, [May contain /+/- =: Titanium DIoxide/CI77891, Iron Oxides/CI77491/77492/77499].

PACKAGE LABEL

Jafra

Tester Always Color Stay-On Makeup SPF 10

Muestrario de Maquillaje Facial de Larga Duracion *FPS 10

Contains: 10 testers at .27 Fl Oz each

Contenido: 10 Pazs de 8 ml c/u / 80 ml